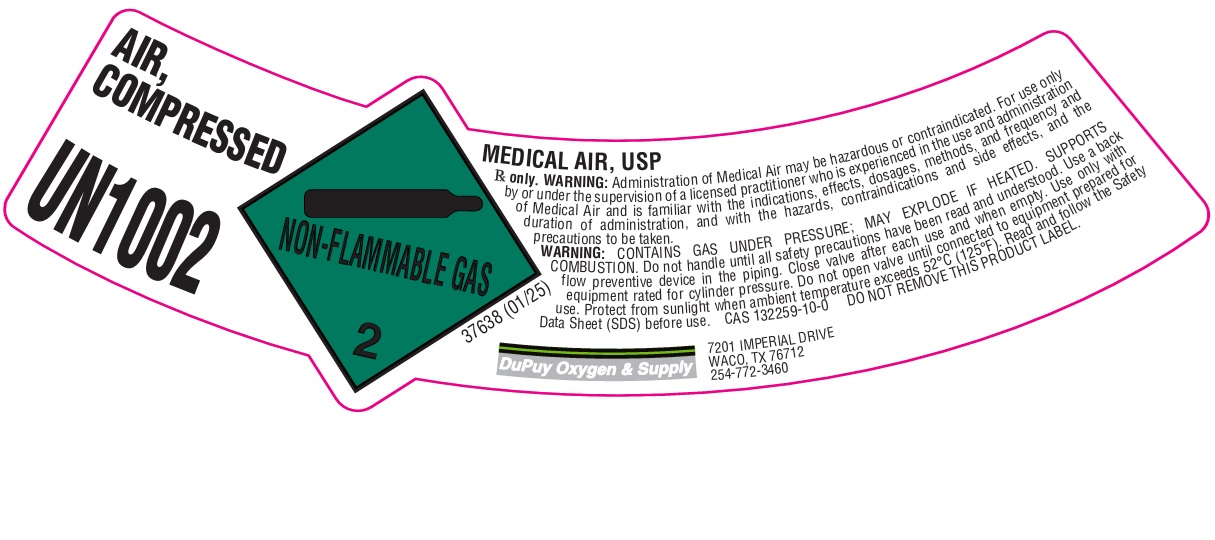 DRUG LABEL: Air
NDC: 50554-007 | Form: GAS
Manufacturer: DuPuy Oxygen & Supply Company, Inc.
Category: prescription | Type: HUMAN PRESCRIPTION DRUG LABEL
Date: 20260225

ACTIVE INGREDIENTS: AIR 1000 mL/1 L

Air

PACKAGE LABEL

AIR, COMPRESSED

UN1002

MEDICAL AIR, USP

Rx only. WARNING: Administration of Medical Air may be hazardous or contaminated. For use only by or under the supervision of a licensed practitioner who is experienced in the use and administration of Medical Air and is familiar with the indications, effects, dosages, methods, and frequency and duration of administration, and with the hazards, contraindications and side effects, and the precautions to be taken.

WARNING: CONTAINS GAS UNDER PRESSURE; MAY EXPLODE IF HEATED. SUPPORTS COMBUSTION. Do not handle until all safety precautions have been read and understood. Use a back flow preventive device in the piping. Close valve after each use and when empty. Use only with equipment rated for cylinder pressure. Do not open valve until connected to equipment prepared for use. Protect from sunlight when ambient temperature exceeds 52 C (125 F). Read and follow the Safety Data Sheet (SDS) before use. CAS 132259-10-0 DO NOT REMOVE THIS PRODUCT LABEL.

DuPuy Oxygen & Supply

7201 IMPERIAL DRIVE

WACO, TX 76712

254-772-3460